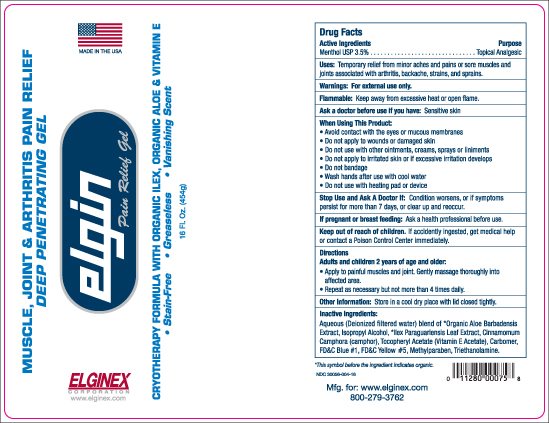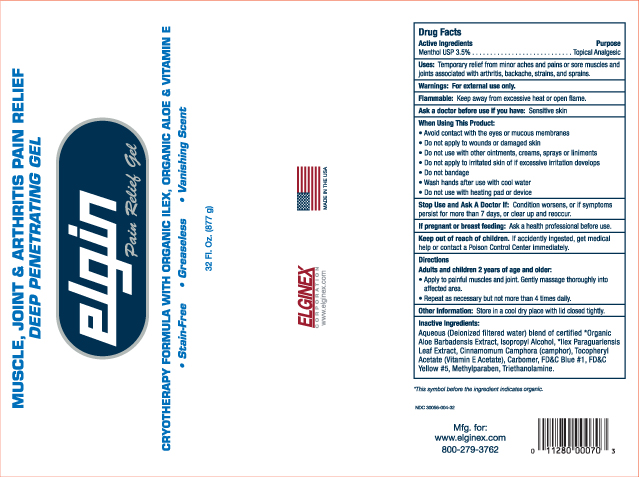 DRUG LABEL: Elgin Pain Relief
NDC: 30056-004 | Form: GEL
Manufacturer: Eco-Logics, Inc.
Category: otc | Type: HUMAN OTC DRUG LABEL
Date: 20250116

ACTIVE INGREDIENTS: MENTHOL 35 mg/1 g
INACTIVE INGREDIENTS: CAMPHOR (NATURAL); METHYLPARABEN; TROLAMINE; FD&C YELLOW NO. 5; ALOE VERA LEAF; ISOPROPYL ALCOHOL; ILEX PARAGUARIENSIS LEAF; ALPHA-TOCOPHEROL; FD&C BLUE NO. 1; WATER; CARBOMER HOMOPOLYMER TYPE C (ALLYL PENTAERYTHRITOL CROSSLINKED)

OTC-ACTIVE INGREDIENT SECTION

Active Ingedients Purpose

Menthol USP 3.5%................... Topical Analgesic

Purpose

Menthol USP 3.5%Topical Analgesic

Uses

Temporary relief from minor aches and pains of sore muscles and joints associated with arthritis, backache, strains, and sprains.

Warning

For external Use only.

Directions

ADirections:

Adults and children 2 years of age and older:

Apply to painful muscles and joints. Genthly massage thtoughly into affected areas.

Repeat as necessary but not more than 4 times daily.

Ask doctor before use if you:

Ask a doctor before use if you have sensitive skin.

When using this product

Avoid contact with the eyes or mucous membranes.

Do not apply to wounds or damaged skin.

Do not use with other ointments, creams, sprays or linaments.

Do nopt apply to irrated skin or ifexcessive irration develops.

Do not bandage.

Wash hands after use with cool water.

Do not use with heating pad or device.

Stop Use and Ask a Doctor if:

Stop use and Ask doctor If: Condition worsens, or if symptoms persist for more than 7 days, or clear up and reoccur.

Keep out of reach of children. If accidentally ingested, get medical help or contact Poison Control Center.

Directions

Adults and children 2 years of age and older:

Apply to painful muscles and joints. Genthly massage throughly into affected area.

Repeat as necessary but not more than 4 times daily.

Other information

Other information: Store in a cool dry place with lid closed tightly.

Inactive Ingredients

Aqueou(Deionized water) blend of certified * Organic Aloe Barbadensis Extract, Isopropyl Alcohol, *Ilex Paraguariensis Leaf Extract, Cinnamomum Camphora (camphor), Tocopheryl Acetate (Vitamin E Acetate) Carbomer, FDC Blue #1, FDC Yellow#5, Methylparaben, Triethanolamine.

If pregnant or breast feeding:

If pregrant or breast feeding. Ask a health professional before use.